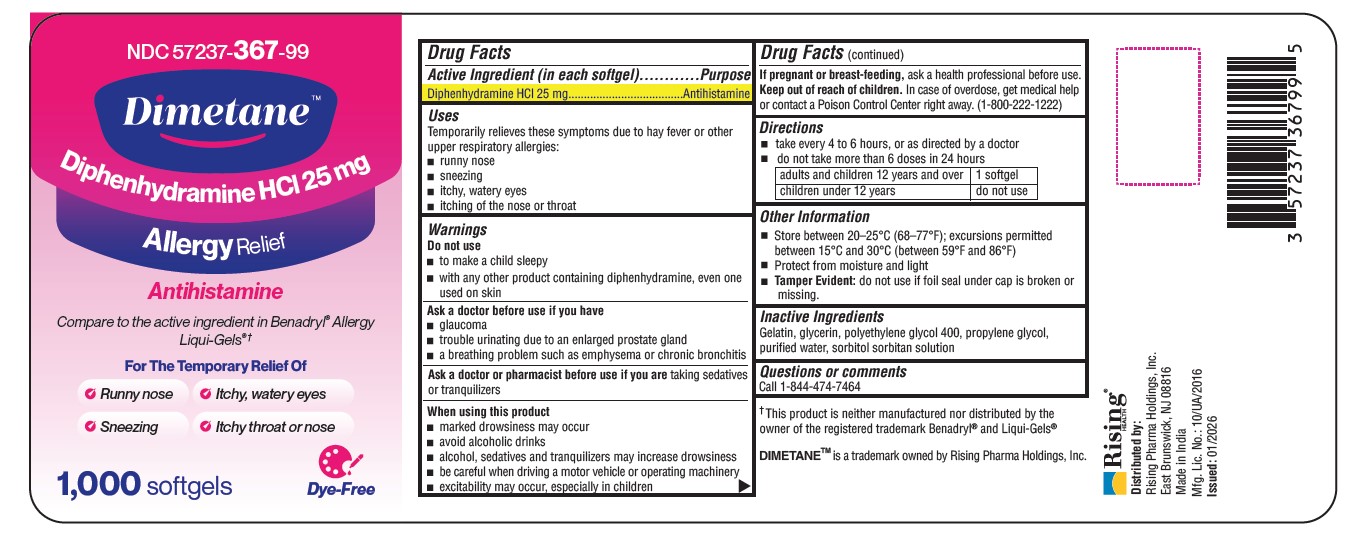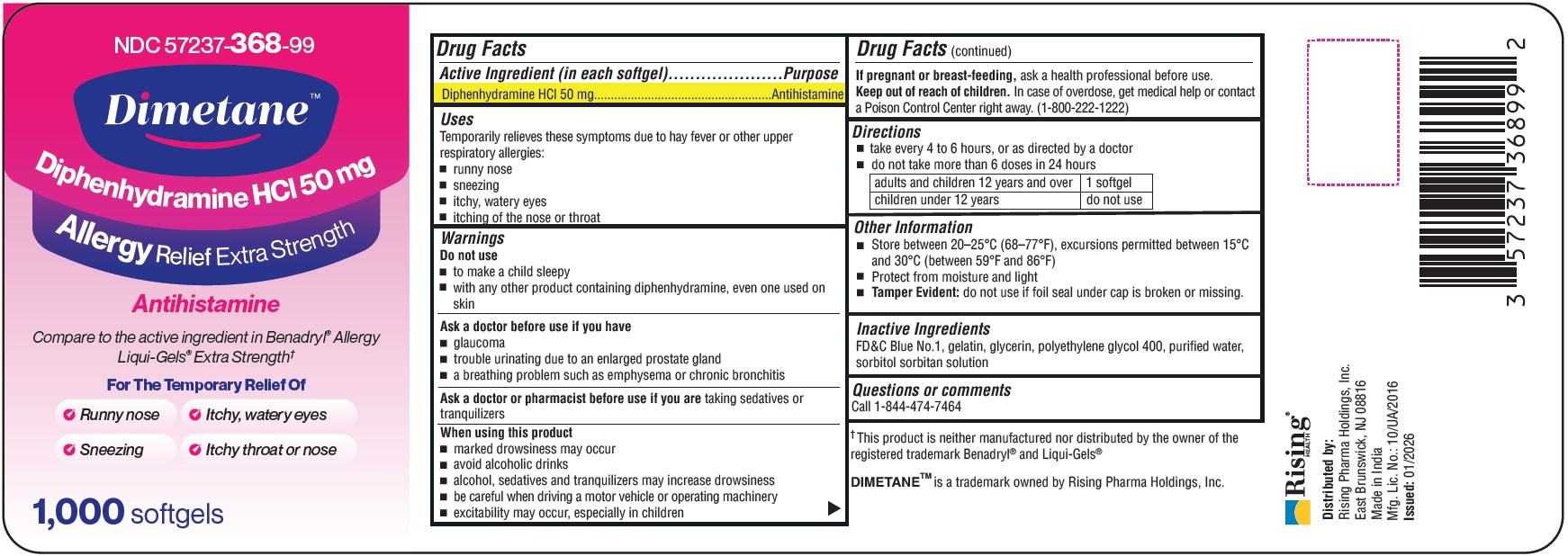 DRUG LABEL: Dimetane
NDC: 57237-367 | Form: CAPSULE, LIQUID FILLED
Manufacturer: Rising Pharma Holdings, Inc.
Category: otc | Type: HUMAN OTC DRUG LABEL
Date: 20260119

ACTIVE INGREDIENTS: DIPHENHYDRAMINE HYDROCHLORIDE 25 mg/1 1
INACTIVE INGREDIENTS: GELATIN, UNSPECIFIED; GLYCERIN; POLYETHYLENE GLYCOL 400; PROPYLENE GLYCOL; WATER; SORBITOL

Dimetane™ Allergy Relief -25mg
Dimetane™ Allergy Relief Extra Strength -50mg

Drug Facts

Active Ingredient (in each softgel)

Diphenhydramine HCl 25 mg & 50 mg

Purpose

Antihistamine

Uses

Temporarily relieves these symptoms due to hay fever or other upper respiratory allergies:

- runny nose
- sneezing
- itchy, watery eyes
- itching of the nose or throat

Warnings

Do not use

- to make a child sleepy
- with any other product containing diphenhydramine, even one used on skin

Ask a doctor before use if you have

- glaucoma
- trouble urinating due to an enlarged prostate gland
- a breathing problem such as emphysema or chronic bronchitis

Ask a doctor or pharmacist before use if you are taking sedatives or tranquilizers

When using this product

- marked drowsiness may occur
- avoid alcoholic drinks
- alcohol, sedatives and tranquilizers may increase drowsiness
- be careful when driving a motor vehicle or operating machinery
- excitability may occur, especially in children

PREGNANCY OR BREAST FEEDING

If pregnant or breast-feeding, ask a health professional before use.

Keep out of reach of children. In case of overdose, get medical help or contact a Poison Control Center right away. (1-800-222-1222)

Directions

- take every 4 to 6 hours, or as directed by a doctor
- do not take more than 6 doses in 24 hours

adults and children 12 years and over 1 softgel

children under 12 years do not use

Other Information

- Store between 20-25°C (68-77°F), excursions permitted between 15°C and 30°C (between 59°F and 86°F)
- Protect from moisture and light.
- Tamper Evident: do not use if foil seal under cap is broken or missing.

Inactive Ingredients

25mg:- Gelatin, glycerin, polyethylene glycol 400, propylene glycol, purified water, sorbitol sorbitan solution

50mg:- FD&C Blue No. 1, gelatin, glycerin, polyethylene glycol 400, purified water, sorbitol sorbitan solution

Questions or comments

Call 1-877-474-7464

†This product is neither manufactured nor distributed by the owner of the registered trademark Benadryl® and Liqui-Gels®

DIMETANE TM is a trademark owned by Rising Pharma Holdings, Inc.

Distributed by:

Rising Pharma Holdings, Inc.

East Brunswick, NJ 08816

Made in India

Mfg. Lic. No.: 10/UA/2016

PRINCIPAL DISPLAY PANEL

NDC 57237-367-99

Dimetane TM

Diphenhydramine HCl 25 mg

Allergy Relief

Antihistamine

Compare to the active ingredient in Benadryl ®Allergy Liqui-Gels ®†

For the Temporary Relief of

Runny Nose Itchy, watery eyes, Sneezing, Itchy throat or nose

NDC 57237-368-99

Dimetane TM

Diphenhydramine HCl 50 mg

Allergy Relief Extra Strength

Antihistamine

Compare to the active ingredient in Benadryl ® Allergy Liqui-Gels ®* Extra Strength®†

For the Temporary Relief of

Runny Nose Itchy, watery eyes, Sneezing, Itchy throat or nose